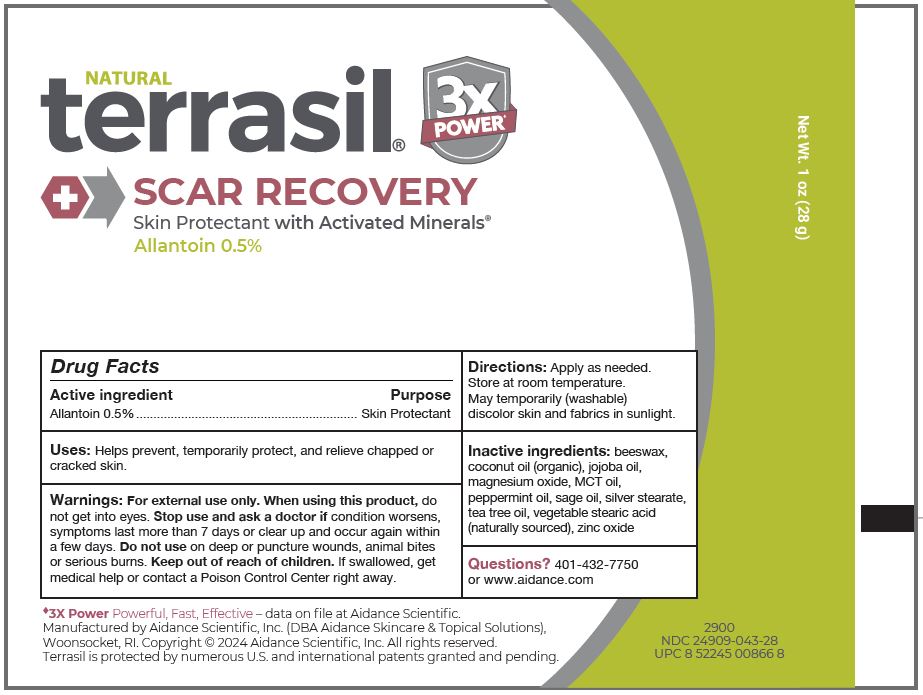 DRUG LABEL: terrasil Scar Recovery
NDC: 24909-043 | Form: OINTMENT
Manufacturer: Aidance Scientific, Inc., DBA Aidance Skincare & Topical Solutions
Category: otc | Type: HUMAN OTC DRUG LABEL
Date: 20241226

ACTIVE INGREDIENTS: ALLANTOIN 0.5 g/100 g
INACTIVE INGREDIENTS: SILVER STEARATE; COCONUT OIL; ZINC OXIDE; TEA TREE OIL; SAGE OIL; PALM OIL; PEPPERMINT OIL; JOJOBA OIL; MAGNESIUM OXIDE; STEARIC ACID

24909-043 terrasil Scar Recovery

Active Ingredient

Allantoin 0.5%

Purpose

Skin Protectant

Uses

Helps prevent, temporarily protect, and relieve chapped or cracked skin.

Warnings

For external use only.

When using this product, do not get into eyes.

Stop use and ask a doctor if condition worsens, symptoms last more than 7 days or clear up and occur again within a few days.

Do not use on deep or puncture wounds, animal bites or serious burns.

Keep out of reach of children.

OTHER SAFETY INFORMATION

If swallowed, get medical help or contact a Poison Control Center right away.

Directions

Apply as needed. Store at room temperature. May temporarily (washable) discolor skin and fabrics in sunlight.

Inactive ingredients

beeswax, coconut oil (organic), jojoba oil, magnesium oxide, MCT oil, peppermint oil, sage oil, silver stearate, tea tree oil, vegetable stearic acid (naturally sourced), zinc oxide

Questions?

401-432-7750 or www.aidance.com